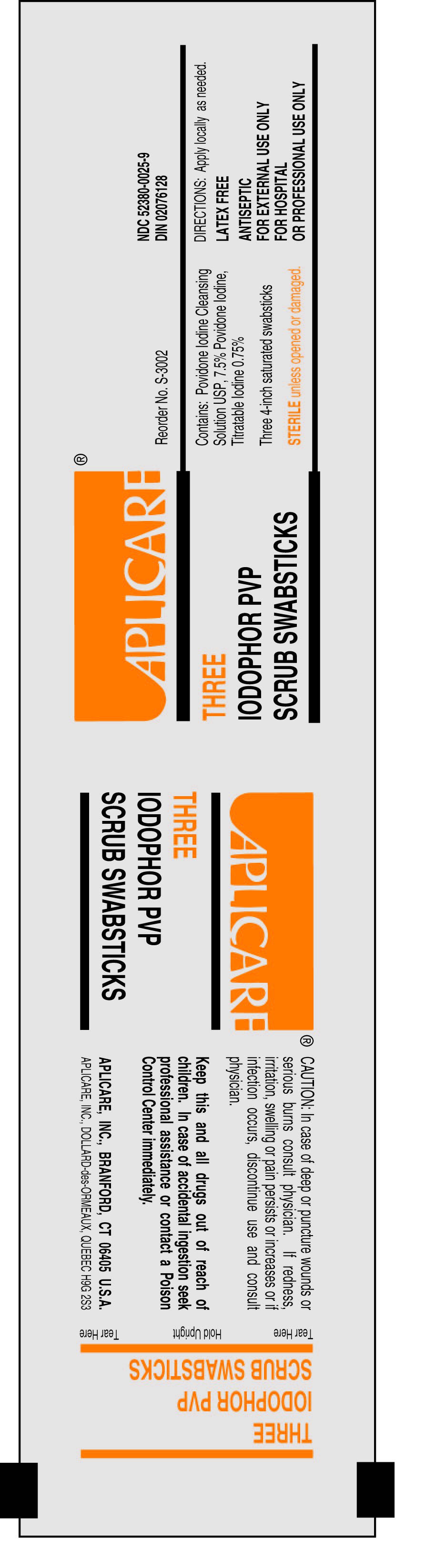 DRUG LABEL: Aplicare Povidone-iodine Scrub
NDC: 52380-0025 | Form: SOLUTION
Manufacturer: Aplicare, Inc.
Category: otc | Type: HUMAN OTC DRUG LABEL
Date: 20100105

ACTIVE INGREDIENTS: POVIDONE-IODINE 8.1 g/100 g
INACTIVE INGREDIENTS: SODIUM PHOSPHATE, DIBASIC; ANHYDROUS CITRIC ACID; SODIUM HYDROXIDE; NONOXYNOL-9; AMMONIUM NONOXYNOL-4 SULFATE; WATER

Drug Facts

PACKAGE LABEL

Povidone-iodine Scrub Swabstick Packet

ACTIVE INGREDIENT

Povidone-iodine

PURPOSE

Antiseptic

Stop use and ask a doctor if

- redness, irritation, swelling or pain persists or increases
- infection occurs
- injuries are deep or puncture wounds or serious burns

Do not use if allergic to iodine

Keep out of reach of children. In case of accidental ingestion, seek professional assistance or consult a poison control center immediately.

Questions or comments?

1 800 760-3236 (Mon to Fri 8:30 AM - 5:00 PM EST)